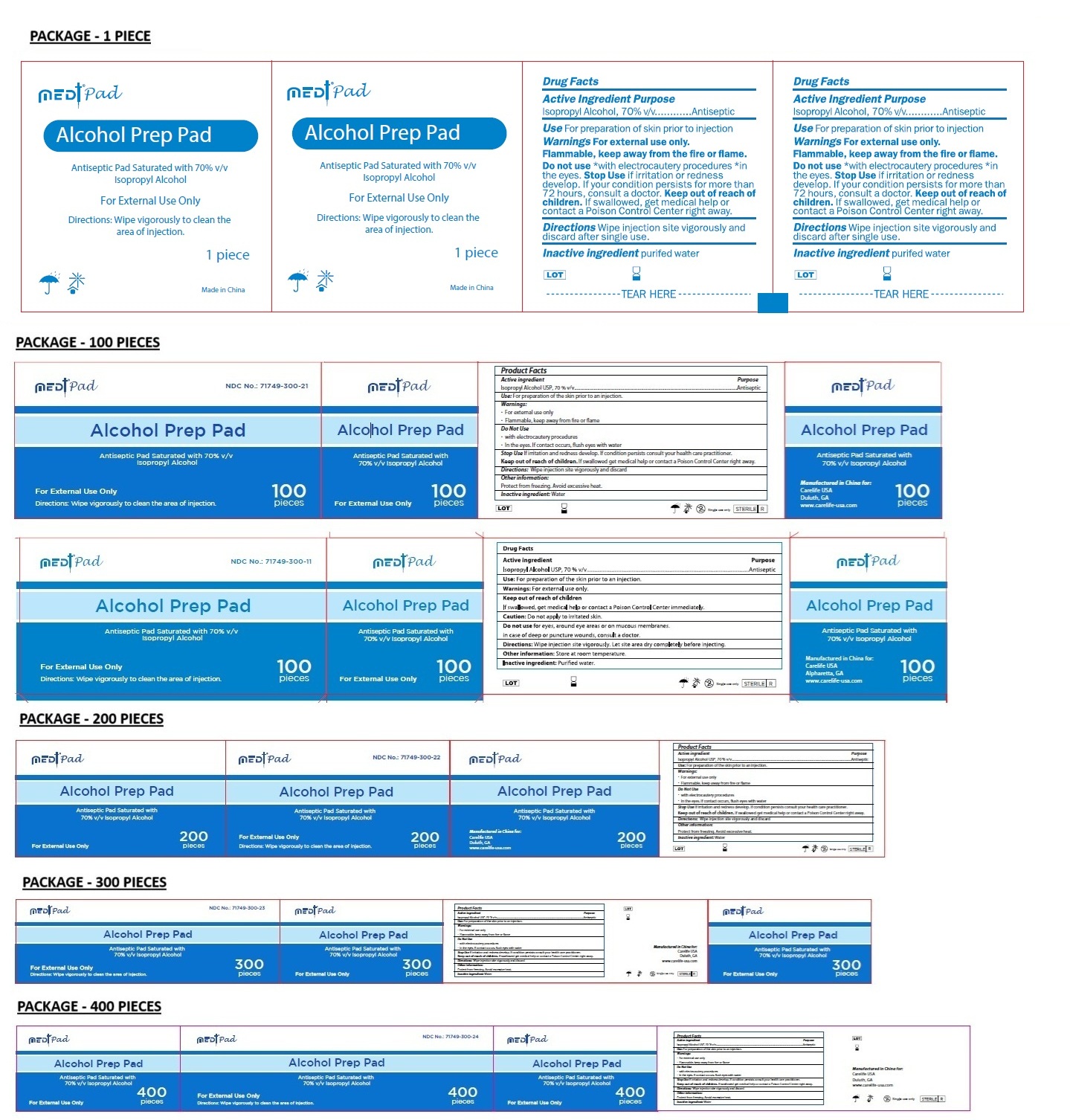 DRUG LABEL: Medt Pad
NDC: 71749-300 | Form: SWAB
Manufacturer: Carelife (USA) Inc.
Category: otc | Type: HUMAN OTC DRUG LABEL
Date: 20260115

ACTIVE INGREDIENTS: ISOPROPYL ALCOHOL 70 mL/100 mL
INACTIVE INGREDIENTS: WATER

Medt Pad

Active Ingredients

Isopropyl Alcohol 70%

Purpose

Antiseptic

Use

For preparation of the skin prior to an injection

Warnings

• For external use only
• Flammable, keep away from the fire or flame

Do Not Use
• with electrocautery procedures
• In the eyes. If contact occurs, flush eyes with water

Stop Use If irritation or redness develop.
If your condition persists consult your health care practitioner.

Keep out of reach of children. If swallowed get medical help or contact a Poison Control Center right away.

Directions

• Wipe injection site vigorously and discard

Other Information

• Protect from freezing. Avoid excessive heat.

Inactive Ingredient

Water

Alcohol Prep Pad

Antiseptic Pad Saturated with 70% v/v Isopropyl Alcohol

Directions: Wipe vigorously to clean the area of injection.

Manufactured in China for:
Carelife USA
Duluth, GA
www.carelife-usa.com